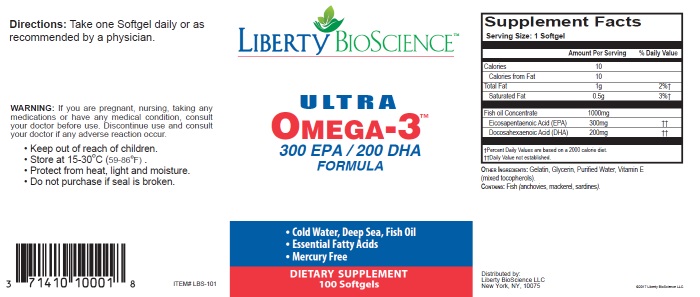 DRUG LABEL: Ultra Omega 3
NDC: 71410-100 | Form: CAPSULE, GELATIN COATED
Manufacturer: Liberty Bioscience LLC
Category: other | Type: DIETARY SUPPLEMENT
Date: 20170501

ACTIVE INGREDIENTS: Icosapent 300 mg/1 1; Doconexent 200 mg/1 1; FISH OIL 1000 mg/1 1
INACTIVE INGREDIENTS: Gelatin; glycerin; tocopherol; mackerel, unspecified; sardine, unspecified; anchovy, unspecified

Ultra Omega 3™

Supplement Facts

Dietary Supplement

Serving Size: 1 Softgel

Servings Per Container: 100

 | Amount Per Serving | % Daily Value
Calories | 10
Calories from Fat | 10
Total Fat | 1 g | 2% [Percent Daily Values are based on a 2,000 calorie diet.]
Saturated Fat | 0.5 g | 3%
Fish body oil EPA (eicosapentaenoic acid) 300 mg DHA (docosahexaenoic acid) 200 mg | 1,000 mg | [Daily value not established.]

Other ingredients: Gelatin, glycerin, Purified Water, Vitamin E

Contains fish (mackerel, sardines, anchovy)

Directions

Take 1 or 2 softgel daily, or as directed by a physician.

Warning

If you are pregnant, nursing, taking any medications or have any medical condition, consult your doctor before use.

SAFE HANDLING WARNING

- Keep out of the reach of children.
- Store at 15-30°C (59-86°F).
- Protect from heat, light and moisture.
- Do not purchase if seal is broken.

Distributed By:
Liberty BioScience™
401 E. 80th Street
Suite 8B
New York, NY, 10075

HEALTH CLAIM

Help Support: Healthy Joints, Healthy Cholesterol

PRINCIPAL DISPLAY PANEL - 100 Capsule Bottle Label

ULTRA OMEGA 3™

EPA 300 / DHA 200 FORMULA

COLD WATER, DEEP SEA, FISH OIL

ESSENTIAL FATTY ACIDS

MERCURY FREE

100 Softgels

Dietary Supplement